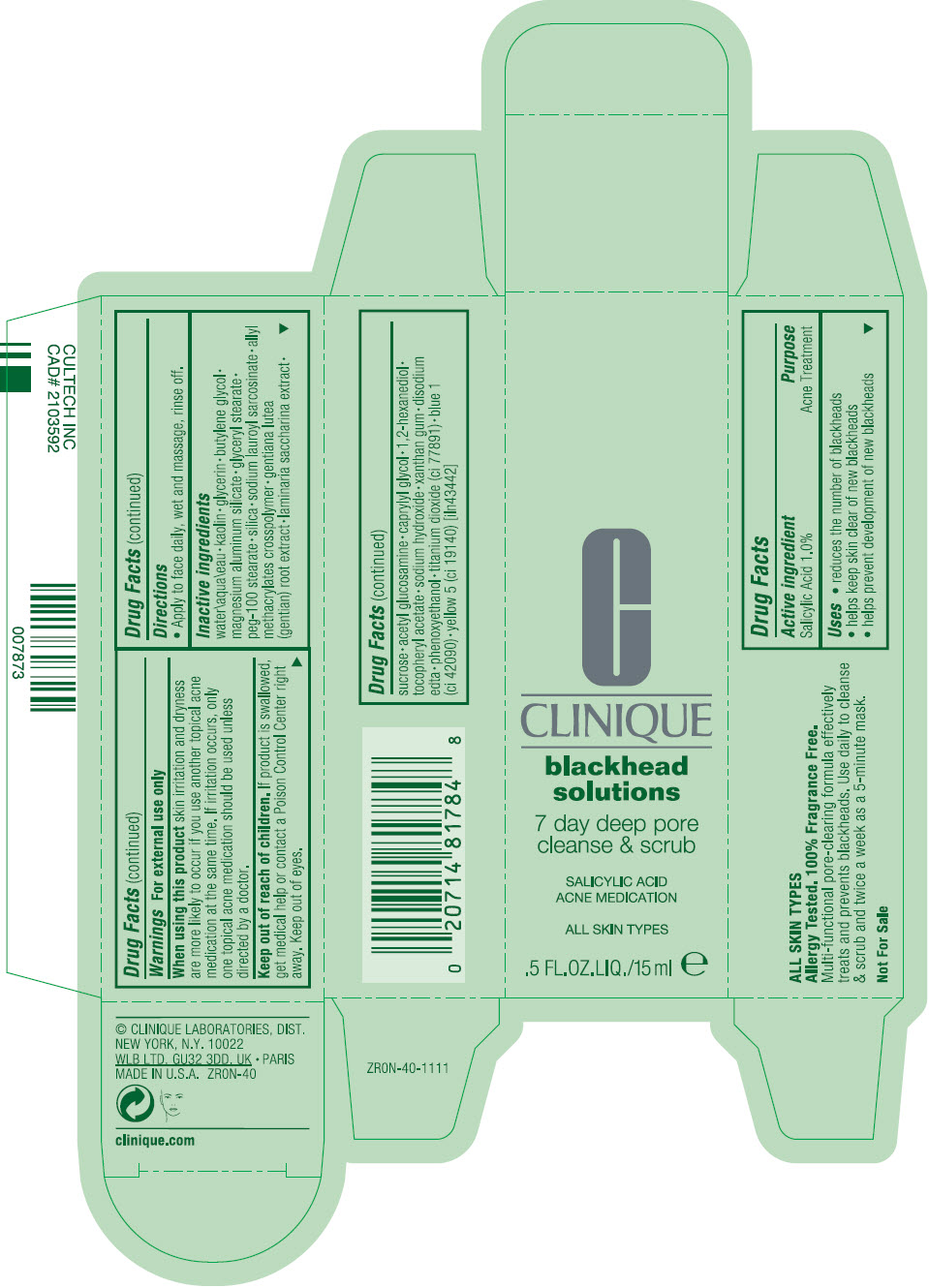 DRUG LABEL: blackhead solutions 7 day deep pore cleanse and scrub acne medication
NDC: 49527-062 | Form: CREAM
Manufacturer: CLINIQUE LABORATORIES LLC
Category: otc | Type: HUMAN OTC DRUG LABEL
Date: 20241225

ACTIVE INGREDIENTS: SALICYLIC ACID 10 mg/1 mL
INACTIVE INGREDIENTS: WATER; KAOLIN; GLYCERIN; BUTYLENE GLYCOL; MAGNESIUM ALUMINUM SILICATE; GLYCERYL MONOSTEARATE; PEG-100 STEARATE; SILICON DIOXIDE; SODIUM LAUROYL SARCOSINATE; SUCROSE; N-ACETYLGLUCOSAMINE; CAPRYLYL GLYCOL; 1,2-HEXANEDIOL; SODIUM HYDROXIDE; XANTHAN GUM; EDETATE DISODIUM ANHYDROUS; PHENOXYETHANOL; TITANIUM DIOXIDE; FD&C BLUE NO. 1; FD&C YELLOW NO. 5

blackhead solutions 7 day deep pore cleanse and scrub acne medication

Drug Facts

Active ingredient

Salicylic Acid 1.0%

Purpose

Acne Treatment

Uses

- reduces the number of blackheads
- helps keep skin clear of new blackheads
- helps prevent development of new blackheads

Warnings

For external use only

When using this product skin irritation and dryness are more likely to occur if you use another topical acne medication at the same time. If irritation occurs, only one topical acne medication should be used unless directed by a doctor.

Keep out of reach of children. If product is swallowed, get medical help or contact a Poison Control Center right away. Keep out of eyes.

Directions

- Apply to face daily, wet and massage, rinse off.

Inactive ingredients

water\aqua\eau • kaolin • glycerin • butylene glycol • magnesium aluminum silicate • glyceryl stearate • peg-100 stearate • silica • sodium lauroyl sarcosinate • allyl methacrylates crosspolymer • gentiana lutea (gentian) root extract • laminaria saccharina extract • sucrose • acetyl glucosamine • caprylyl glycol • 1,2-hexanediol • tocopheryl acetate • sodium hydroxide • xanthan gum • disodium edta • phenoxyethanol • titanium dioxide (ci 77891) • blue 1 (ci 42090) • yellow 5 (ci 19140) [iln43442]

PRINCIPAL DISPLAY PANEL - 15 ml Bottle Carton

CLINIQUE

blackhead
solutions

7 day deep pore
cleanse & scrub

SALICYLIC ACID
ACNE MEDICATION

ALL SKIN TYPES

.5 FL.OZ.LIQ./15 ml e